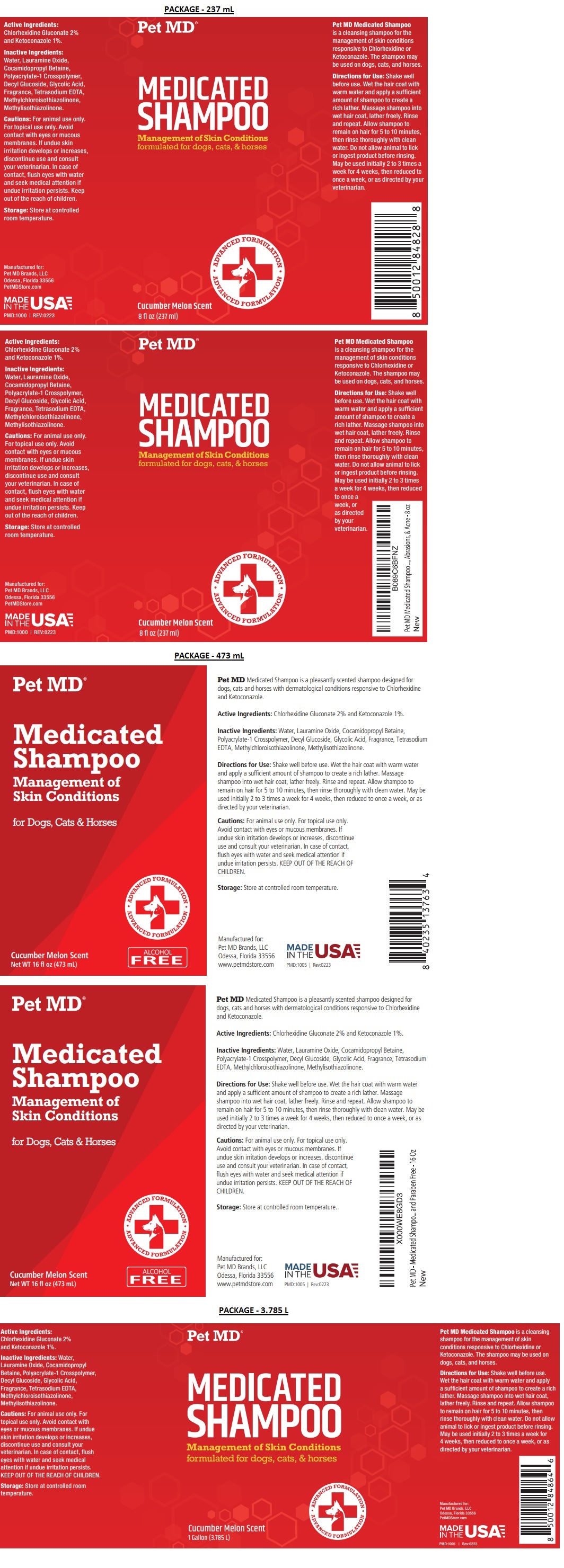 DRUG LABEL: Pet MD Medicated
NDC: 86090-003 | Form: SHAMPOO
Manufacturer: Pet MD Brands, LLC
Category: animal | Type: OTC ANIMAL DRUG LABEL
Date: 20230907

ACTIVE INGREDIENTS: CHLORHEXIDINE GLUCONATE 2 g/100 mL; KETOCONAZOLE 1 g/100 mL
INACTIVE INGREDIENTS: WATER; LAURAMINE OXIDE; COCAMIDOPROPYL BETAINE; POLYACRYLATE-1 CROSSPOLYMER; DECYL GLUCOSIDE; GLYCOLIC ACID; EDETATE SODIUM; METHYLCHLOROISOTHIAZOLINONE; METHYLISOTHIAZOLINONE

Pet MD® Medicated Shampoo

Active Ingredients:

Chlorhexidine Gluconate 2% and Ketoconazole 1%.

INDICATIONS AND USAGE

Pet MD Medicated Shampoo is a pleasantly scented shampoo designed for dogs, cats and horses with dermatological conditions responsive to Chlorhexidine and Ketoconazole.

Inactive Ingredients:

Water, Lauramine Oxide, Cocamidopropyl Betaine, Polyacrylate-1 Crosspolymer, Decyl Glucoside, Glycolic Acid, Fragrance, Tetrasodium EDTA, Methylchloroisothiazolinone, Methylisothiazolinone.

Directions for Use:

Shake well before use. Wet the hair coat with warm water and apply a sufficient amount of shampoo to create a rich lather. Massage shampoo into wet hair coat, lather freely. Rinse and repeat. Allow shampoo to remain on hair for 5 to 10 minutes, then rinse thoroughly with clean water. May be used initially 2 to 3 times a week for 4 weeks, then reduced to once a week, or as directed by your veterinarian.

Cautions:

For animal use only. For topical use only. Avoid contact with eyes or mucous membranes. If undue skin irritation develops or increases, discontinue use and consult your veterinarian. In case of contact, flush eyes with water and seek medical attention if undue irritation persists. KEEP OUT OF THE REACH OF CHILDREN.

Storage:

Store at controlled room temperature.

Management of Skin Conditions

for Dogs, Cats & Horses

ADVANCED FORMULATION

ALCOHOL FREE

Cucumber Melon Scent

Manufactured for:
Pet MD Brands, LLC
Odessa, Florida 33556
www.petmdstore.com

MADE IN THE USA

Paraben Free